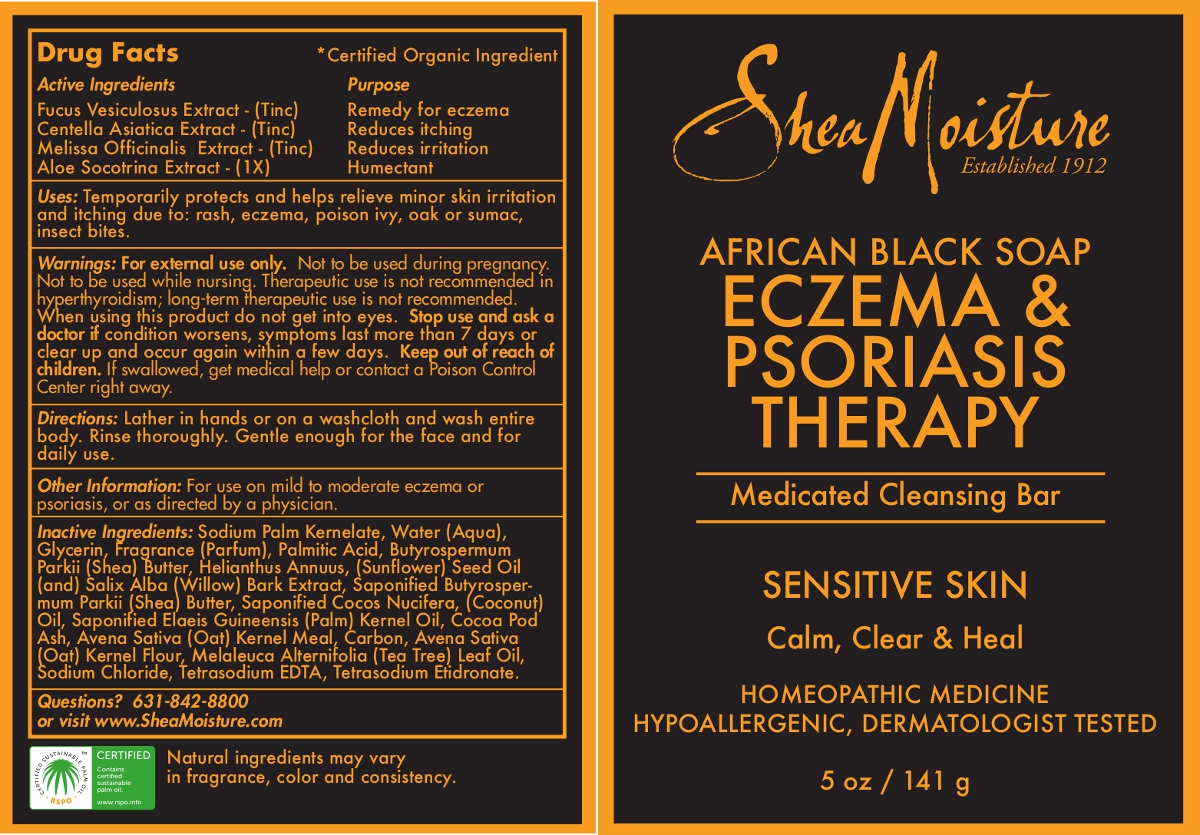 DRUG LABEL: Eczema and Psoriasis Therapy
NDC: 58666-3122 | Form: SOAP
Manufacturer: Sundial Group LLC
Category: homeopathic | Type: HUMAN OTC DRUG LABEL
Date: 20130625

ACTIVE INGREDIENTS: FUCUS VESICULOSUS 1 [hp_X]/1 g; CENTELLA ASIATICA 1 [hp_X]/1 g; MELISSA OFFICINALIS 1 [hp_X]/1 g; ALOE 1 [hp_X]/1 g
INACTIVE INGREDIENTS: SODIUM PALM KERNELATE; WATER; GLYCERIN; PALMITIC ACID; SHEA BUTTER; SUNFLOWER OIL; SALIX ALBA BARK; COCONUT OIL; PALM OIL; COCOA; OATMEAL; ACTIVATED CHARCOAL; TEA TREE OIL; SODIUM CHLORIDE; EDETATE SODIUM; ETIDRONATE TETRASODIUM

Eczema and Psoriasis Therapy

Drug Facts

ACTIVE INGREDIENT

Active Ingredients | Purpose
Fucus Vesiculosus Extract - (Tinc) | Remedy for eczema
Centella Asiatica Extract - (Tinc) | Reduces itching
Melissa Officinalis Extract - (Tinc) | Reduces irritation
Aloe Socotrina Extract - (1X) | Humectant

INDICATIONS AND USAGE

Uses: Temporarily protects and helps relieve minor skin irritation and itching due to: rash, eczema, poison ivy, oak or sumac, insect bites.

WARNINGS

ASK DOCTOR

Warnings: For external use only.

PREGNANCY OR BREAST FEEDING

Not to be used during pregnancy. Not to be used while nursing.

WARNINGS

Therapeutic use is not recommended in hyperthyroidism; long-term therapeutic use is not recommended. When using this product do not get into eyes.

Stop use and ask a doctor if condition worsens, symptoms last more than 7 days or clear up and occur again within a few days.

Keep out of reach of children.

WARNINGS

If swallowed, get medical help or contact a Poison Control Center right away.

DOSAGE AND ADMINISTRATION

Directions: Lather in hands or on a washcloth and wash entire body. Rinse thoroughly. Gentle enough for the face and for daily use.

Other information: For use on mild to moderate eczema or psoriasis, or as directed by a physician.

INACTIVE INGREDIENT

Inactive ingredients: Sodium Palm Kernelate, Water (Aqua), Glycerin, Fragrance (Parfum), Palmitic Acid, Butyrospermum Parkii (Shea) Butter, Helianthus Annuus, (Sunflower) Seed Oil (and) Salix Alba (Willow) Bark Extract, Saponified Butyrospermum Parkii (Shea) Butter, Saponified Cocos Nucifera, (Coconut) Oil, Saponified Elaeis Guineensis (Palm) Kernel Oil, Cocoa Pod Ash, Avena Sativa (Oat) Kernel Meal, Carbon, Avena Sativa (Oat) Kernel Flour, Melaleuca Alternifolia (Tea Tree) Leaf Oil, Sodium Chloride, Tetrasodium EDTA, Tetrasodium Etidronate.

*Certified Organic Ingredient

QUESTIONS

Questions? 631-842-8800 or visit www.SheaMoisture.com